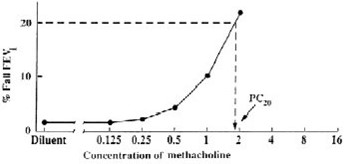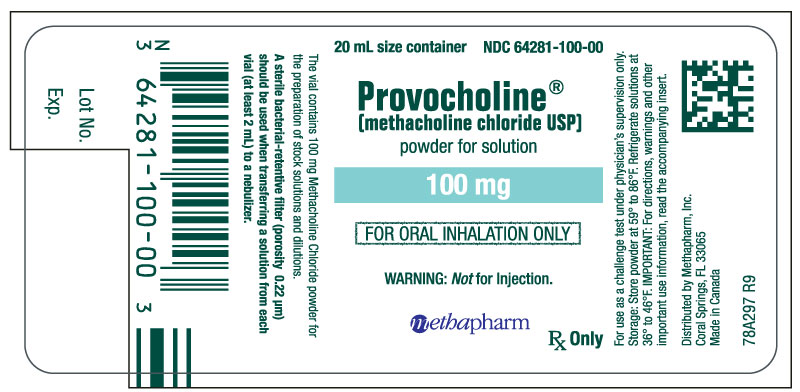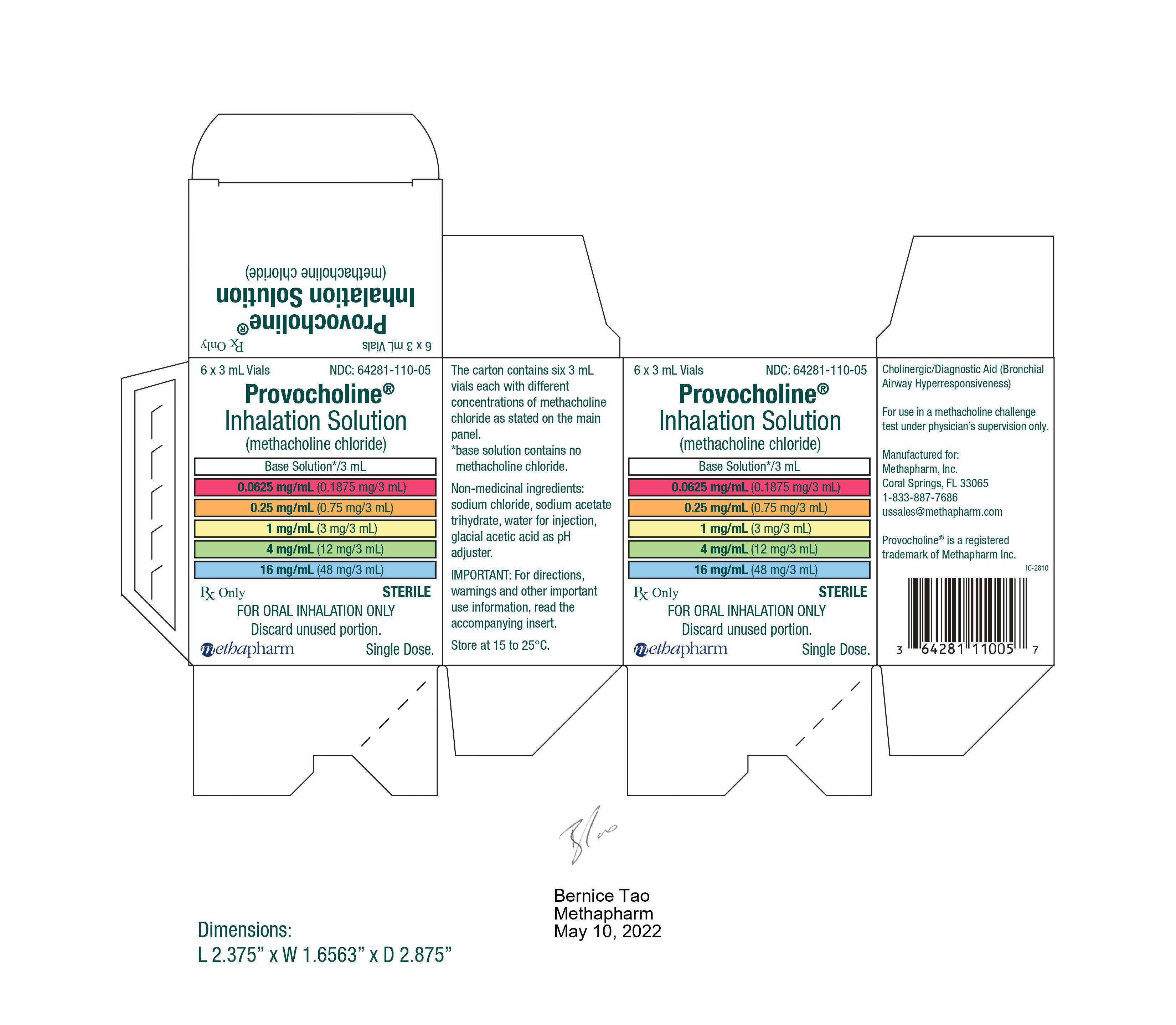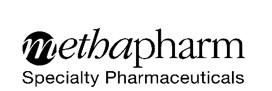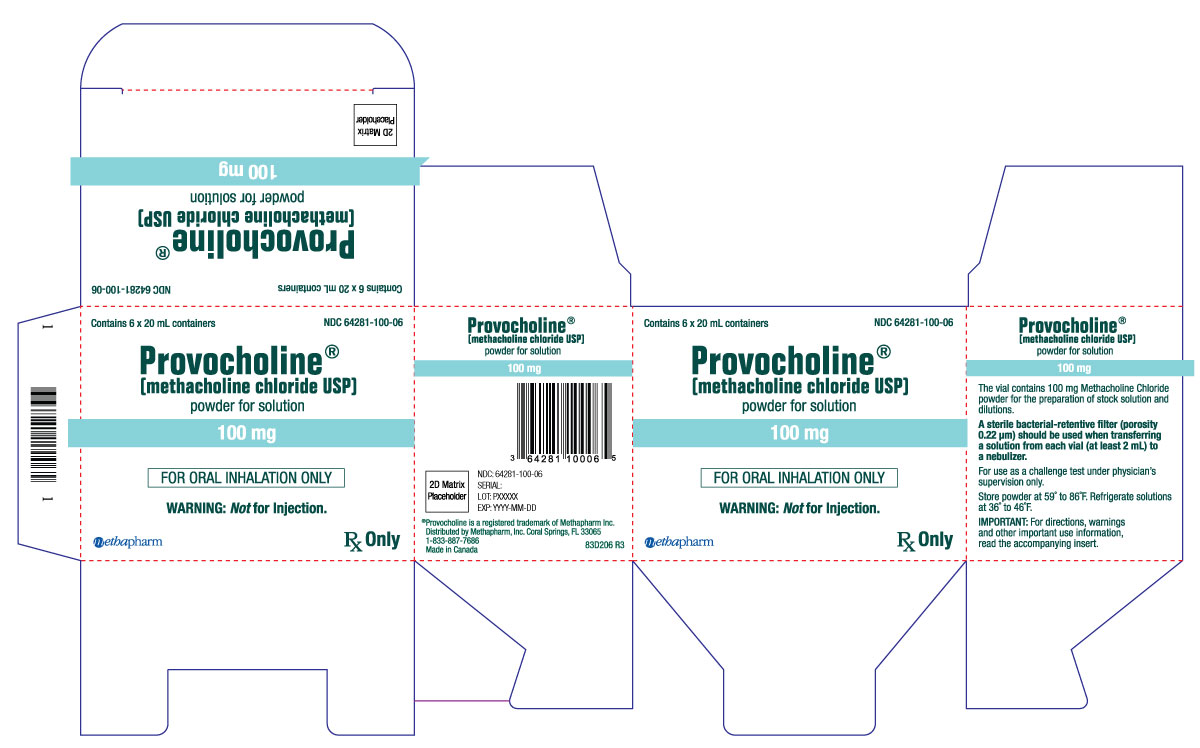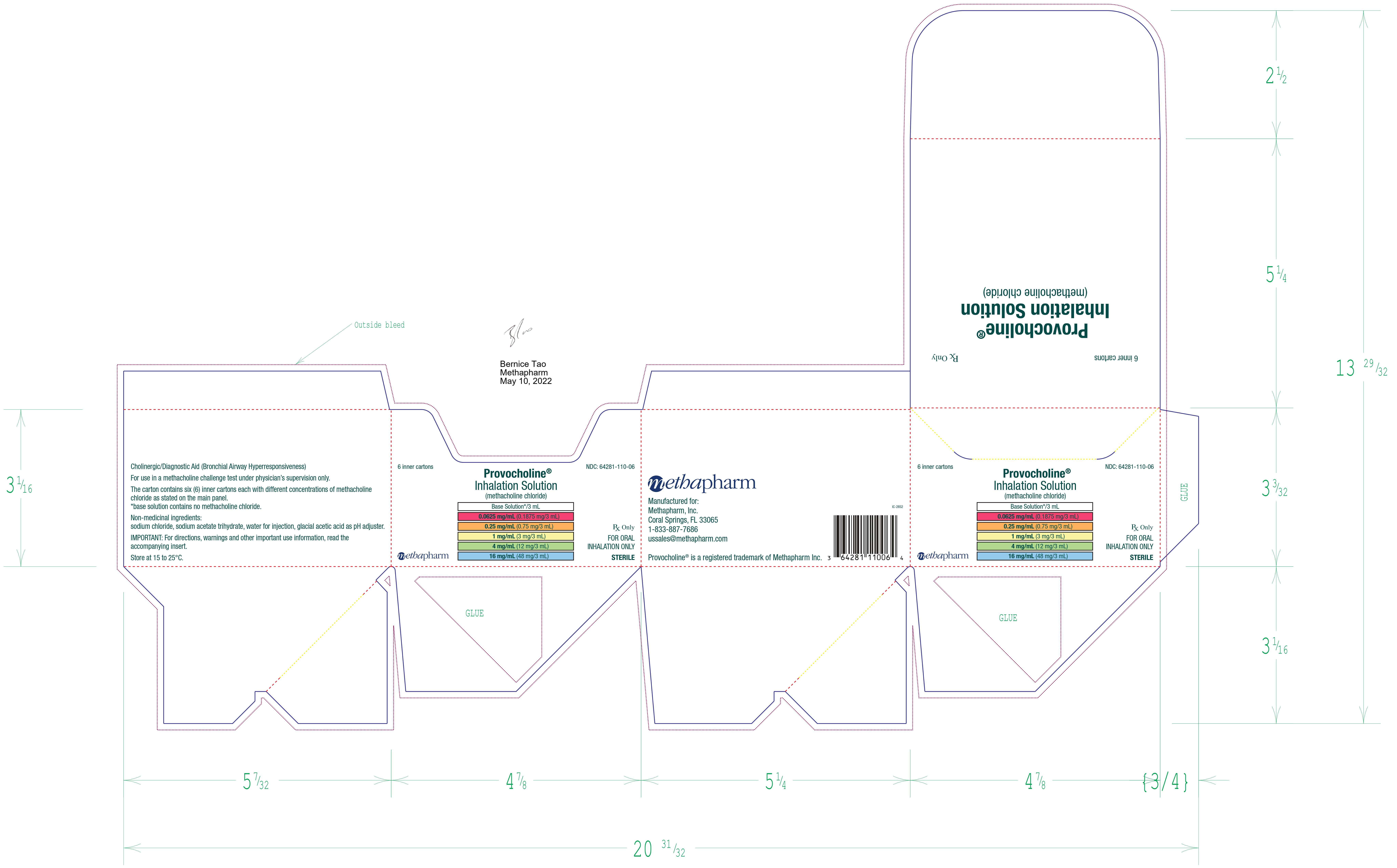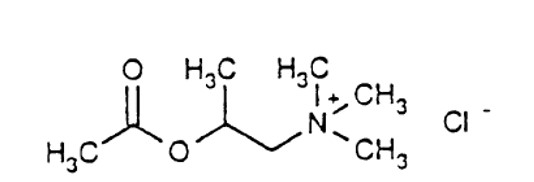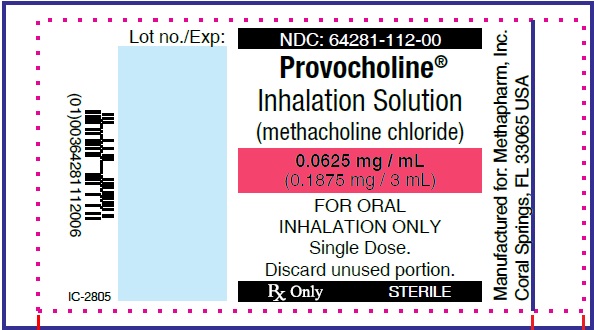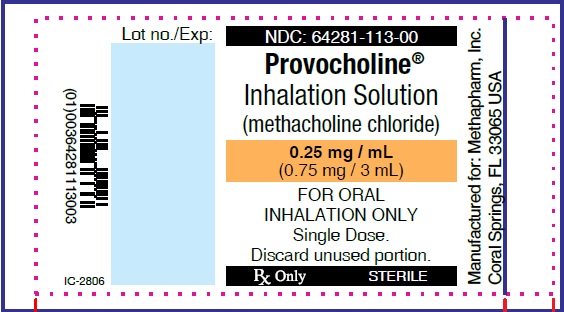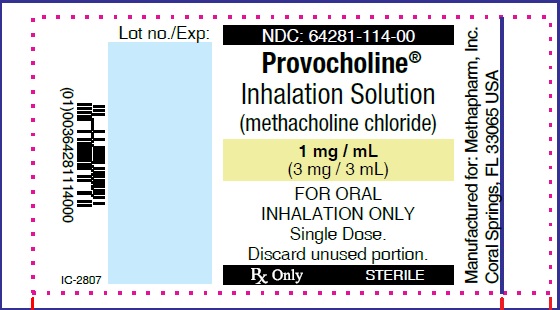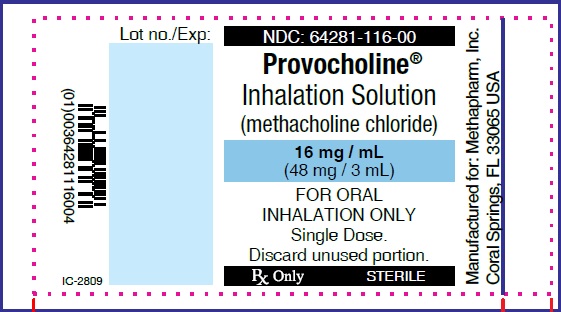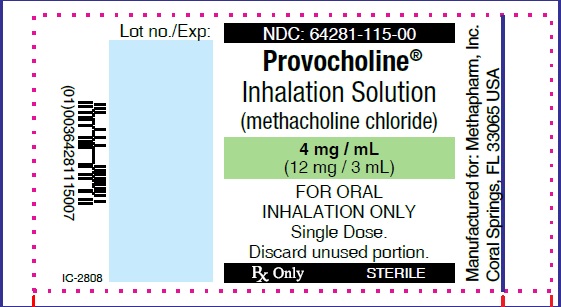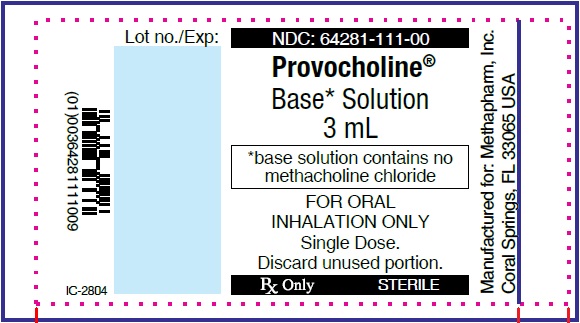 DRUG LABEL: Provocholine
NDC: 64281-100 | Form: POWDER, FOR SOLUTION
Manufacturer: Methapharm Inc.
Category: prescription | Type: HUMAN PRESCRIPTION DRUG LABEL
Date: 20250116

ACTIVE INGREDIENTS: METHACHOLINE CHLORIDE 100 mg/100 mg

HIGHLIGHTS OF PRESCRIBING INFORMATION

These highlights do not include all the information needed to use PROVOCHOLINE® safely and effectively.
See full prescribing information for PROVOCHOLINE®.
PROVOCHOLINE® (methacholine chloride) for inhalation solution, for oral inhalation use
PROVOCHOLINE® (methacholine chloride) inhalation solution, for oral inhalation use
Initial U.S. Approval: 1986

WARNING: SEVERE BRONCHOCONSTRICTION

See full prescribing information for complete boxed warning.

- Severe bronchoconstriction can result from Provocholine administration (including the lowest dose) (5.1)
- Use of Provocholine is contraindicated in pediatric and adult patients with baseline FEV1 < 60% predicted or adults
- with FEV1 < 1.5 L (5.1)
- Use of Provocholine is not recommended in patients with clinically apparent asthma or wheezing (5.1)
- If severe bronchoconstriction occurs, reverse immediately with a rapid-acting inhaled bronchodilator agent (β-Agonist) (5.1)

1 INDICATIONS AND USAGE

Provocholine, a cholinergic agonist used in a methacholine challenge test, is indicated for the diagnosis of bronchial airway hyperreactivity in adults and pediatric patients five years of age and older who do not have clinically apparent asthma (1)

2 DOSAGE AND ADMINISTRATION

- The methacholine challenge test should be conducted in a pulmonary function laboratory or clinic, by adequately trained personnel, for safety and accuracy (2.1)
- Determine baseline FEV1 values to assess whether a patient is able to undergo the methacholine challenge test (2.1)
- Recommended dosage(s) of Provocholine in the Methacholine Challenge Test is administration of increasing concentrations of Provocholine solution via nebulization (2.2)
- Administer using either the 5-Breath Dosimeter Dosing Method or the 2-Minute Tidal Breathing Dosing Method with the doubling or quadrupling stepwise protocols (2.4, 2.5)
- See the Full Prescribing Information for the required reconstitution and dilution procedures prior to use (2.3)
- See the Full Prescribing Information for the calculation and interpretation of the results (2.6)

3 DOSAGE FORMS AND STRENGTHS

• For inhalation solution: 100 mg methacholine chloride powder in amber glass vials (3)
• Inhalation solution: base solution (contains no methacholine chloride), 0.0625 mg/mL, 0.25 mg/mL, 1 mg/mL, 4 mg/mL, and 16 mg/mL, each containing 3 mL of the concentrations of methacholine chloride per vial in a kit (3)

4 CONTRAINDICATIONS

- Known hypersensitivity to methacholine chloride or other parasympathomimetic agents (4)
- Baseline FEV1 <60% predicted (adults or children) or <1.5 L (adults) (4)

5 WARNINGS AND PRECAUTIONS

Healthcare provider and any other personnel involved in the administration of the methacholine challenge test should take precautions to minimize inhalation of Provocholine powder and nebulized aerosol (5.2)

6 ADVERSE REACTIONS

Adverse reactions associated with Provocholine include headache, throat irritation, light-headedness and itching (6)

To report SUSPECTED ADVERSE REACTIONS, contact Methapharm at 1-866-701-4636 or call FDA at 1-800-FDA-1088 or visit www.fda.gov/medwatch

7 DRUG INTERACTIONS

- Beta-Adrenergic Blockers: May impair reversal of Provocholine-caused bronchoconstriction (7)
- Beta-Agonists, Anticholinergics, and Theophylline: Inhibit response to Provocholine; therefore, hold these drugs prior to Provocholine use (7)
- Oral or Inhaled Corticosteroids, and Inhaled Cromyoglycate: May decrease response to Provocholine (7)

8 USE IN SPECIFIC POPULATIONS

Pregnancy: Provocholine is not recommended (8.1)

FULL PRESCRIBING INFORMATION

WARNING: SEVERE BRONCHOCONSTRICTION

Severe bronchoconstriction can result from Provocholine administration (including the lowest dose). The use of Provocholine is contraindicated in pediatric and adult patients with baseline FEV1 < 60% predicted or adults with FEV1 < 1.5 L. Because of the potential for severe bronchoconstriction, the use of Provocholine in patients with clinically apparent asthma or wheezing is not recommended [see Warnings and Precautions (5.1)].

Emergency equipment and medication should be immediately available to treat acute respiratory distress. If severe bronchoconstriction occurs, reverse immediately with a rapid-acting inhaled bronchodilator agent (β-agonist) [see Warnings and Precautions (5.1)].

If baseline spirometry is not performed or is measured inaccurately, the initial FEV1 may be underestimated. In this situation, decreases in FEV1 may not be detected after administration of escalating Provocholine doses, which may result in administration of unnecessary higher doses and an increased risk for excessive bronchoconstriction [see Warnings and Precautions (5.1)].

1 INDICATIONS AND USAGE

Provocholine, used in a methacholine challenge test, is indicated for the diagnosis of bronchial airway hyperreactivity in adults and pediatric patients five years of age and older who do not have clinically apparent asthma.

2 DOSAGE AND ADMINISTRATION

2.1 Methacholine Challenge Test Overview

- Provocholine should be administered in a methacholine challenge test in a pulmonary function laboratory or clinic, by adequately trained personnel, for safety and accuracy, and should be performed only under the responsibility of a healthcare practitioner trained in and thoroughly familiar with all aspects of the technique of the test and the management of respiratory distress. Emergency medication and equipment should be immediately available to treat acute respiratory distress.
- Only consider Provocholine use in patients on chronic asthma drugs if the accuracy of the asthma diagnosis is in doubt. In these patients, only administer Provocholine if spirometry is normal after supervised withdrawal of the asthma drugs.
- Provocholine is not recommended for use in patients with clinically apparent asthma or wheezing.
- Before starting a methacholine challenge test, baseline spirometry must be performed. For a patient to be able to undergo the test, he or she must present with baseline FEV1 (Forced Expiratory Volume in 1 second) greater than or equal to 60% of the predicted value (in adults and children) and greater than or equal to 1.5 L (in adults).
- Do not use Provocholine in pediatric and adult patients with baseline FEV1 < 60% predicted or in adults with FEV1 < 1.5 L [see Contraindications (4) and Warnings and Precautions (5.1)].
- At commencement of the methacholine challenge test and prior to nebulization with Provocholine dose(s), FEV1 must be measured following exposure to nebulized diluent or base solution (contains no methacholine chloride) to obtain the post-diluent FEV1 [see Dosage and Administration (2.4, 2.5)].
- Provocholine powder for inhalation solution requires reconstitution and dilution before use (see Reconstitution and Dilution Prior to Administration (2.3)).
- Provocholine inhalation solution (in a ready-to-use kit) does not require reconstitution and/or dilution.
- Administer Provocholine by oral inhalation using either the 5-Breath Dosimeter Dosing Method or the 2-Minute Tidal Breathing Dosing Method with the doubling or quadrupling stepwise protocols [see Dosage and Administration (2.4, 2.5)].
- Discard any unused solution from the nebulizer after each administration.
- May use Provocholine with or without meals.
- The methacholine challenge test is considered positive if there is a reduction in FEV1 of 20% or more from post-diluent FEV1. The test should be stopped at this point. The reduction value must be calculated and recorded before starting the test with Provocholine (see Calculation and Interpretation of Methacholine Challenge Test Results (2.6)).
- An inhaled β agonist must be administered after a methacholine challenge test with Provocholine to expedite the return of the FEV1 to baseline and to relieve any discomfort of the subject. Most patients revert to normal pulmonary function within 10 to 20 minutes following administration of a β agonist.

2.2 Recommended Dosage

The recommended dosage of Provocholine powder for inhalation solution (require reconstitution and dilution) or inhalation solution (in a ready-to-use kit) used in the methacholine challenge test administered via nebulization in adult and pediatric patients (5 years or older) is increasing concentrations of methacholine chloride solutions using either doubling or quadrupling dosing concentrations. Please refer to Table 3 for the doubling or quadrupling dosing concentrations.

2.3 Reconstitution and Dilution Prior to Administration

1. Provocholine Powder for Inhalation Solution requires reconstitution before use (see Tables 1 and 2):

Add 6.25 mL of 0.9% Sodium Chloride Injection (0.9% saline) or 0.9% Sodium Chloride Injection with 0.4% phenol (0.9% saline with 0.4% phenol) to the supplied vials containing 100 mg of Provocholine powder. Shake the vial to obtain a clear solution.

2. Dilute the reconstituted Provocholine solution:

Using sterile, empty USP Type 1 borosilicate glass vials, dilute the reconstituted Provocholine solution with 0.9% saline or 0.9% saline with 0.4% phenol either by doubling the concentration (see Table 1) or quadrupling the concentration (see Table 2). After adding the diluent, shake each vial to obtain a clear solution. Use the same diluent to prepare all concentrations

3. Use a sterile bacterial-retentive filter (porosity 0.22 µm) when transferring the reconstituted or diluted solution from each vial (at least 2 mL) to a nebulizer.

4. Refrigerate the reconstituted and diluted solutions at 36oF to 46oF (2oC to 8oC) for up to 2 weeks. Since the temperature of the solution affects nebulizer output, solutions should be taken out of the refrigerator and allowed to equilibrate to room temperature (approximately 30 minutes) before use.

Table 1: Reconstitution and Dilution of Supplied Provocholine powder for inhalation solution: Doubling Concentrations

TAKE | ADD 0.9% Saline or 0.9% Saline with 0.4% Phenol | Concentration (Total Volume) after reconstitution or dilution
100 mg of Provocholine Powder in one supplied vial | 6.25 mL | 16 mg/mL (6.25 mL) (Solution A)
3 mL of Solution A | 3 mL | 8 mg/mL (6 mL) (Solution B)
3 mL of Solution B | 3 mL | 4 mg/mL (6 mL) (Solution C)
3 mL of Solution C | 3 mL | 2 mg/mL (6 mL) (Solution D)
3 mL of Solution D | 3 mL | 1 mg/mL (6 mL) (Solution E)
3 mL of Solution E | 3 mL | 0.5 mg/mL (6 mL) (Solution F)
3 mL of Solution F | 3 mL | 0.25 mg/mL (6 mL) (Solution G)
3 mL of Solution G | 3 mL | 0.125 mg/mL (6 mL) (Solution H)
3 mL of Solution H | 3 mL | 0.0625 mg/mL (6 mL) (Solution I)

Table 2: Reconstitution and Dilution of Supplied Provocholine powder for inhalation solution: Quadrupling Concentrations

TAKE | ADD 0.9% Saline or 0.9% Saline with 0.4% Phenol | Concentration (Total Volume) after reconstitution or dilution
100 mg of Provocholine Powder in one supplied vial | 6.25 mL | 16 mg/mL (6.25 mL) (Solution 1)
3 mL of Solution 1 | 9 mL | 4 mg/mL (12 mL) (Solution 2)
3 mL of Solution 2 | 9 mL | 1 mg/mL (12 mL) (Solution 3)
3 mL of Solution 3 | 9 mL | 0.25 mg/mL (12 mL) (Solution 4)
3 mL of Solution 4 | 9 mL | 0.0625 mg/mL (12 mL) (Solution 5)

2.4 Administration with the Five (5)-Breath Dosimeter Dosing Method in Patients 5 Years of Age and Older

Prior to administering the Provocholine dose(s), determine the post-diluent FEV1 value required for the methacholine challenge test.

Administration of the Diluent or Base to Obtain Post-Diluent FEV1 Value

1. For the Provocholine powder for inhalation solution:

Using a 3 mL syringe and needle, draw up 2 to 3 mL of the same diluent used to reconstitute the Provocholine Powder (0.9% saline or 0.9% saline with 0.4% phenol) and dispense into the nebulizer using a sterile bacterial-retentive filter (porosity 0.22 µm).

For the Provocholine inhalation solution:

Dispense the contents of a vial containing the base solution (contains no methacholine chloride) into the nebulizer.

2. Instruct the patient to hold the nebulizer upright with the mouthpiece in his/her mouth. The patient should wear a nose clip while inhaling from the nebulizer.
3. At the end of exhalation during tidal breathing (functional residual capacity), instruct the patient to inhale slowly and deeply through the mouthpiece. Trigger the dosimeter soon after oral inhalation begins. Encourage the patient to continue inhaling slowly (about 5 seconds to complete the inhalation) and to hold the breath at total lung capacity (TLC) for another 5 seconds.

4. Repeat Step 3 for a total of five inspiratory capacity inhalations. Take no more than 2 minutes to perform these 5 inhalations.
5. Perform spirometry and measure the FEV1 30 and 90 seconds after the fifth inhalation from the nebulizer to obtain the post-diluent FEV1 value. These values may be left at ambient (spirometer) temperature pressure saturated (ATPS). If the FEV1 value is not of acceptable quality, repeat the procedure. If the post-diluent FEV1 falls by ≥ 20% from baseline FEV1, do not give further inhalations and proceed to Step 8. If the post-diluent FEV1 falls by < 20% from baseline FEV1, continue to Step 6.

Administration of Provocholine in a Methacholine Challenge Test

6. For the Provocholine powder for inhalation:

Using a 3 mL syringe and needle, draw up the recommended Provocholine concentration (see Table 3) that was prepared using either the doubling or quadrupling dose method and dispense into the nebulizer using a sterile bacterial-retentive filter (porosity 0.22 µm). See Tables 1 and 2 for preparation of the Provocholine powder for inhalation solution.

Table 3: Recommended Provocholine Dose(s) By Nebulization [Doubling Dose(s) or Quadrupling Dose(s)]

Doubling Dose Increments
Provocholine Concentration | Provocholine Dose*
0.0625 mg/mL (Solution I) | 1.484 mcg
0.125 mg/mL (Solution H) | 2.969 mcg
0.25 mg/mL (Solution G) | 5.938 mcg
0.5 mg/mL (Solution F) | 11.875 mcg
1 mg/mL (Solution E) | 23.75 mcg
2 mg/mL (Solution D) | 47.5 mcg
4 mg/mL (Solution C) | 95 mcg
8 mg/mL (Solution B) | 190 mcg
16 mg/mL (Solution A) | 380 mcg
Quadrupling Dose Increments
Provocholine Concentration | Provocholine Dose*
0.0625 mg/mL (Solution 5) | 1.484 mcg
0.25 mg/mL (Solution 4) | 5.938 mcg
1 mg/mL (Solution 3) | 23.75 mcg
4 mg/mL (Solution 2) | 95 mcg
16 mg/mL (Solution 1) | 380 mcg

* Dose delivered based on the drug output of the English Wright Nebulizer and the duration of inhalation (2 minutes).

For the Provocholine inhalation solution:

Dispense the contents of a vial of the appropriate Provocholine concentration, starting with the lowest dose, into the nebulizer. The Provocholine solution concentrations, 0.0625 mg/mL, 0.25 mg/mL, 1 mg/mL, 4 mg/mL, and 16 mg/mL, provided in the kit are ready-to-use. No further dilution is required.

7. Repeat steps 2 through 5 for each Provocholine concentration, emptying the nebulizer between each concentration. To keep the cumulative effect of Provocholine relatively constant, the time interval between the commencement of two subsequent concentrations should be kept to 5 minutes.

8. Stop dosing if the FEV1 has fallen by ≥ 20% from the post-diluent FEV1, or the highest Provocholine concentration (16 mg/mL) has been administered (whichever comes first). Do not administer additional Provocholine concentrations if severe bronchoconstriction occurs [see Warnings and Precautions (5.1)].

9. After the test is completed, administer an inhaled β-agonist to the patient to expedite the return of the FEV1 to within 90% of baseline and to relieve any discomfort (the majority of patients revert to normal pulmonary function within 5 minutes after β-agonist administration; in contrast the majority of patients revert to normal pulmonary function within 30-45 minutes without β-agonist administration). Wait 10 minutes and measure the FEV1 and Vital Capacity. Patients should not be allowed to leave the laboratory until their FEV1 has returned to within 90% of baseline.

10. After the test, wash and clean reusable nebulizers thoroughly according to manufacturer’s recommendations.

2.5 Administration with the Two (2)-Minute Tidal Breathing Dosing Method in Patients 5 Years of Age and Older

Administer the diluent and the Provocholine dose(s) using the English Wright nebulizer or other suitable nebulizer as long as the device output and particle size are characterized.
Prior to administering the Provocholine dose(s), determine the post-diluent FEV1 required for the methacholine challenge test.

Administration of the Diluent or Base Solution to Obtain Post-Diluent FEV1 Value

1. For the Provocholine powder for inhalation solution:

Using a 3 mL syringe and needle, draw up 2 to 3 mL of the same diluent used to reconstitute the Provocholine powder (0.9% saline or 0.9% saline with 0.4% phenol) and dispense into the nebulizer using a sterile bacterial-retentive filter (porosity 0.22 µm).

For the Provocholine inhalation solution:

Dispense the contents of a vial containing the base solution (contains no methacholine chloride) into the nebulizer.

2. Instruct the patient to relax and breathe the aerosol quietly (tidal breathing) for 2 minutes of inhalation time.

3. Place the face mask loosely over the nose and mouth or the mouthpiece in the mouth (with a nose clip) of the patient. The patient should hold the nebulizer to avoid warming the solution. Nebulizer should be kept upright and vertical.

4. Start the nebulizer by adjusting the flow meter so that the nebulizer is operating at the calibrated output (0.13 mL/minute for the English Wright nebulizer). Start the stopwatch immediately.

5. After exactly 2 minutes, turn off the flow meter, remove the face mask (or the mouthpiece from the mouth), and discard any remaining solution.

6. Perform spirometry and measure the FEV1 30 and 90 seconds after the end of the inhalation to obtain the post-diluent FEV1. These values may be left at ambient (spirometer) temperature pressure saturated (ATPS). If the FEV1 value is not of acceptable quality, repeat the procedure. If the post-diluent FEV1 falls by ≥ 20% from baseline FEV1, do not give further inhalations and proceed to Step 9. If the post-diluent FEV1 falls by < 20% from baseline FEV1, continue to Step 7.

Administration of Provocholine in a Methacholine Challenge Test

7. For the Provocholine powder for inhalation solution:

Using a 3 mL syringe and needle, draw up the recommended Provocholine dose (see Table 3) using either the doubling or quadrupling dose method and dispense into the nebulizer using a sterile bacterial-retentive filter (porosity 0.22 µm). See Tables 1 and 2 for preparation of the Provocholine powder for inhalation.

For the Provocholine inhalation solution:

Dispense the contents of a vial of the appropriate Provocholine concentration, starting with the lowest dose, into the nebulizer. The Provocholine solution concentrations, 0.0625 mg/mL, 0.25 mg/mL, 1 mg/mL, 4 mg/mL, and 16 mg /mL, provided in the kit are ready-to-use. No further dilution is required.

8. Repeat steps 2 through 6 for each Provocholine dose, emptying the nebulizer between each dose. However, stop dosing if the FEV1 has fallen by ≥ 20% from the post-diluent FEV1 or the highest Provocholine concentration (16 mg/mL) has been administered (whichever comes first). Do not administer additional Provocholine doses if severe bronchoconstriction occurs [see Warnings and Precautions (5.1)].

9. After the test is completed, administer an inhaled β-agonist to the patient to expedite the return of the FEV1 to within 90% of baseline and to relieve any discomfort (the majority of patients revert to normal pulmonary function within 5 minutes after β-agonist administration; in contrast the majority of patients revert to normal pulmonary function within 30-45 minutes without β-agonist administration). Wait 10 minutes and measure the FEV1 and Vital Capacity. Patients should not be allowed to leave the laboratory until their FEV1 has returned to within 90% of baseline.

10. After the test, wash and clean reusable nebulizers thoroughly according to manufacturer’s recommendations and discard disposable nebulizers appropriately.

2.6 Calculation and Interpretation of Methacholine Challenge Test Results

A positive methacholine challenge test is a ≥ 20% reduction in the FEV1 (after Provocholine oral inhalation) compared with the mean post-diluent FEV1. Calculate and record post-diluent FEV1 value before the methacholine challenge test is started. Express airway hyperreactivity as the provocative Provocholine concentration (mg/mL) providing a fall in FEV1 of ≥ 20% (PC20) when the methacholine challenge test is dosed using either the 5-breath dosimeter method or the 2-minute tidal breathing method, or as the provocative Provocholine dose (mcg) providing a fall in FEV1 of ≥ 20% (PD20) when using the 2-minute tidal breathing method.

Calculation of PC20

Calculate PC20 using one of the following methods. Determine the percent decrease in FEV1 using the mean post-diluent FEV1 and the lowest FEV1 post-dose, as shown below:

% fall in FEV1 = mean post-diluent FEV1 - lowest FEV1 post-Provocholine x 100
mean post-diluent FEV1

Method #1

Plot the percent decrease in FEV1 against the increasing methacholine concentration using a log scale and obtain the PC20 by linear interpolation between the last two points, as shown in Figure 1.

Method #2

Alternatively, calculate the PC20 as follows:

PC20 = antilog [log C1+ (log C2 - log C1)(20 - R1)]
(R2- R1)

Where:
• C1 = second last methacholine concentration (< 20% FEV1 decrease)
• C2 = last methacholine concentration (≥ 20% FEV1 decrease)
• R1 = % fall FEV1 after C1
• R2 = % fall FEV1 after C2

Calculation of PD20 (2-minute tidal breathing method only)

Calculate the PD20 as follows:

PD20 = antilog [log D1+ (log D2 - log D1)(20 - R1)]
(R2- R1)

Where:
• D1 = second last Provocholine dose (< 20% FEV1 decrease)
• D2 = last Provocholine dose (≥ 20% FEV1 decrease)
• R1 = % FEV1 decrease after D1
• R2 = % FEV1 decrease after D2

When using the English Wright nebulizer, refer to Table 2 for D1 and D2.

Interpretation of Results

A negative (normal) methacholine challenge result is defined as FEV1 reduction of < 20% after all the doses (doubling or quadrupling dose increments) in Table 1 (for 5-breath dosimeter method) or Table 2 (for the 2-minute tidal breathing method) have been administered.

If asthma drugs are discontinued prior to the methacholine challenge test, consider the possibility of rebound airway hyperreactivity in the interpretation of the test results. The methacholine challenge test may occasionally be falsely positive after an influenza infection or upper respiratory infection, immunizations, in very young or very old patients, in patients with chronic lung disease (e.g., cystic fibrosis, sarcoidosis, tuberculosis, chronic obstructive pulmonary disease), in patients with allergic rhinitis without asthma symptoms, in smokers, or in patients after exposure to air pollutants.

3 DOSAGE FORMS AND STRENGTHS

• For inhalation solution: 100 mg of white to off-white crystalline powder in amber glass vials (powder is reconstituted and then diluted prior to administration)

• Inhalation solution:
o base solution (contains no methacholine chloride/3 mL)
o 0.0625 mg/mL (0.1875 mg/3 mL)
o 0.25 mg/mL (0.75 mg/3 mL)
o 1 mg/mL (3 mg/3 mL)
o 4 mg/mL (12 mg/3 mL)
o 16 mg/mL (48 mg/3 mL)

4 CONTRAINDICATIONS

Provocholine is contraindicated in the following:

- Hypersensitivity to methacholine or other parasympathomimetic agents. Reactions have included rash, itching/swelling (especially of the face/tongue/throat), severe dizziness, trouble breathing.
- Baseline FEV1 < 60% predicted (adults or pediatric patients) or <1.5 L (adults)

5 WARNINGS AND PRECAUTIONS

5.1 Risk of Severe Bronchoconstriction

Severe bronchoconstriction can result from Provocholine administration (including the lowest dose). The use of Provocholine is contraindicated in pediatric and adult patients with baseline FEV1 < 60% predicted or adults with FEV1 < 1.5 L. Emergency equipment and medication should be immediately available to treat acute respiratory distress. Because of the potential for severe bronchoconstriction, the use of Provocholine in patients with clinically apparent asthma or wheezing is not recommended. If severe bronchoconstriction occurs, reverse immediately by the administration of a rapid-acting inhaled β-agonist.

If baseline spirometry is not performed or is measured inaccurately, the initial FEV1 may be underestimated. In this situation, decreases in FEV1 may not be detected after escalating Provocholine doses, which may result in administration of unnecessary higher doses and an increase in the risk for excessive bronchoconstriction.

5.2 Risks to Healthcare Providers Administering Provocholine

The supplied Provocholine powder or the Provocholine nebulized aerosol may cause bronchoconstriction in healthcare providers administering Provocholine in a methacholine challenge test. Healthcare providers and any other personnel involved in the administration of Provocholine should take the following precautionary steps:

- Do not inhale the supplied Provocholine powder
- Do not handle the Provocholine powder if you have asthma or hay fever.
- Apply a low resistance filter to expiratory ports of dosing apparatus, as necessary, to prevent Provocholine release in the room air

5.3 Coexisting Diseases and Conditions

Provocholine is not recommended for patients with uncontrolled hypertension, aortic aneurysm, or history of myocardial infarction or stroke diseases. Patients with epilepsy, vagotonia, peptic ulcer disease, thyroid disease, urinary tract obstruction or other condition that could be adversely affected by a cholinergic agent should undergo methacholine challenge only if the healthcare practitioner considers the benefit to the individual outweighs the potential risks.

6 ADVERSE REACTIONS

The following adverse reactions associated with the use of Provocholine were identified in clinical studies or post marketing reports. Because some of these reactions were reported voluntarily from a population of uncertain size, it is not always possible to reliably estimate their frequency or establish a causal relationship to drug exposure.

Bronchospasm (includes symptoms such as chest tightness, cough or wheezing).

Adverse reactions less commonly associated with Provocholine include headache, throat irritation, light-headedness and itching.

7 DRUG INTERACTIONS

Beta-Adrenergic Blockers

The use of beta-adrenergic blockers may impair reversal of Provocholine-caused bronchoconstriction.

Beta-Agonists, Anticholinergics, and Theophylline
Beta-agonists, anticholinergics, and theophylline inhibit the response of airways to Provocholine; therefore, hold these drugs before Provocholine use for the following duration:

• Short-acting β-agonists (e.g., albuterol): 6 hours
• Long-acting β-agonists (e.g., salmeterol): 36 hours
• Short-acting anti-cholinergics (e.g., ipratropium): 12 hours
• Long-acting anti-cholinergics (e.g., tiotropium): ≥168 hours
• Oral theophylline: 12-48 hours

Oral or Inhaled Corticosteroids, and Inhaled Cromoglycate

Regular use of oral or inhaled corticosteroids and inhaled cromoglycate may acutely decrease bronchial responsiveness to Provocholine. However, these drugs may be continued with Provocholine use.

8 USE IN SPECIFIC POPULATIONS

8.1 Pregnancy

Risk Summary
The available data from published literature on Provocholine use in pregnant women are insufficient to evaluate for a drug-associated risk of major birth defects, miscarriage, or adverse maternal or fetal outcomes. Animal reproduction studies evaluating effects of methacholine chloride on embryofetal development have not been conducted. Diagnosis of bronchial airway hyperreactivity with bronchoprovocation challenge is not recommended for pregnant women because of the potential for hypoxia in the fetus. If bronchial airway hyperreactivity is suspected, consider trial of empiric treatment.

The estimated background risk of major birth defects and miscarriage for the indicated population is unknown. All pregnancies have a background risk of birth defect, loss, or other adverse outcomes. In the United States general population, the estimated background risk of major birth defects and miscarriage in clinically recognized pregnancies is 2 to 4% and 15 to 20%, respectively.

8.2 Lactation

Risk Summary
There are no available data on the presence of methacholine chloride in human milk, the effect on the breastfed infant, or the effect on milk production. The developmental and health benefits of breastfeeding should be considered along with the mother’s clinical need for Provocholine and any potential adverse effects on the breastfed infant from Provocholine or from the underlying maternal condition.

8.4 Pediatric Use

Provocholine is used in a methacholine challenge test for the diagnosis of bronchial airway hyperreactivity in pediatric patients 5 years of age and older who do not have clinically apparent asthma. The safety and effectiveness of Provocholine have not been established in pediatric patients below the age of 5 years.

8.5 Geriatric Use

The diagnosis of bronchial airway hyperreactivity is largely performed in pediatric and younger adult patients. Clinical studies of Provocholine did not include patients 65 years of age or older.

11 DESCRIPTION

Methacholine chloride, the active ingredient of Provocholine, is a parasympathomimetic (cholinergic) bronchoconstrictor agent. Provocholine (methacholine chloride) powder for solution is administered by oral inhalation.

Chemically, methacholine chloride (the active ingredient) is 1-propanaminium, 2-(acetyloxy)-N,N,N,-trimethyl-, chloride. It is a white to practically white deliquescent compound, soluble in water, alcohol and chloroform and insoluble in ether. Aqueous solutions are neutral to litmus.

Methacholine chloride has an empirical formula of C8H18ClNO2, a molecular weight of 195.69, and the following structural formula:

Provocholine Powder for Solution: Each vial of Provocholine contains 100 mg of methacholine chloride powder.

Provocholine Solution for Inhalation Kit (Sterile):
Each kit is packaged in a carton with six plastic vials with twist-off cap each containing 3 mL of the following concentrations of methacholine chloride solution. Each solution also contains: Sodium Acetate Trihydrate, Sodium Chloride, glacial acetic acid as pH adjuster.

a) base solution (contains no methacholine chloride)
b) 0.0625 mg/mL (0.1875 mg/3 mL)
c) 0.25 mg/mL (0.75 mg/3 mL)
d) 1 mg/mL (3 mg/3 mL)
e) 4 mg/mL (12 mg/3 mL)
f) 16 mg/mL (48 mg/3 mL)

12 CLINICAL PHARMACOLOGY

12.1 Mechanism of Action

Methacholine chloride is a cholinergic agonist. Bronchial smooth muscle contains significant parasympathetic (cholinergic) innervation. Methacholine chloride agonizes the muscarinic receptors which eventually induce bronchoconstriction.

12.2 Pharmacodynamics

After oral inhalation of Provocholine, patients with asthma are more sensitive to Provocholine-induced bronchoconstriction than are healthy subjects. This difference in response is the pharmacological basis for Provocholine in the methacholine challenge test.

12.3 Pharmacokinetics

There are no metabolic and pharmacokinetic data available on methacholine chloride.

13 NONCLINICAL TOXICOLOGY

13.1 Carcinogenesis, Mutagenesis, Impairment of Fertility

There have been no studies with methacholine chloride that would permit an evaluation of its carcinogenic or mutagenic potential or of its effect on fertility.

16 HOW SUPPLIED/STORAGE AND HANDLING

How Supplied

- Provocholine (methacholine chloride) Powder for Inhalation Solution: in amber glass vials that contain 100 mg of methacholine chloride powder, white to off-white in color. Cartons have 6 vials (NDC 64281-100-06).

- Provocholine (methacholine chloride) Inhalation Solution Kit (Sterile):

Each kit (NDC: 64281-110-05) contains six (6) plastic vials with twist-off cap each containing 3 mL of different concentrations of methacholine chloride as shown below. Cartons have six (6) kits (NDC 64281-110-06).

a) base solution (contains no methacholine chloride) (NDC: 64281-111-00)
b) 0.0625 mg/mL (0.1875 mg/3 mL) (NDC:64281-112-00)
c) 0.25 mg/mL (0.75 mg/3 mL) (NDC:64281-113-00)
d) 1 mg/mL (3 mg/3 mL) (NDC:64281-114-00)
e) 4 mg/mL (12 mg/3 mL) (NDC:64281-115-00)
f) 16 mg/mL (48 mg/3 mL) (NDC:64281-116-00)

Storage and Handling

- Powder for inhalation solution: Store the supplied powder at 59oF to 86oF (15oC to 30oC). Refrigerate the reconstituted and diluted solutions at 36oF to 46oF (2oC to 8oC) for up to 2 weeks [see Dosage and Administration (2.3)].

- Provocholine inhalation solution kit: Store between 59oF to 86oF (15°C to 30°C). Use immediately upon opening the vial.

17 PATIENT COUNSELING INFORMATION

Risk of Severe Bronchoconstriction
Inform the patient or caregiver that severe bronchoconstriction can result from Provocholine administration [see Warnings and Precautions (5.1)].

Cough, Chest Tightness, or Shortness of Breath
Inform the patient or caregiver that Provocholine may produce mild cough, chest tightness or shortness of breath.

Manufactured for:
Methapharm, Inc.
11772 West Sample Road, Suite 101
Coral Springs, FL,
USA 33065

For more information visit www.methapharmrespiratory.com,
email ussales@methapharm.com
or call 1-833-887-7686.

®Provocholine is a registered trademark of Methapharm Inc.

Revision: December 2022